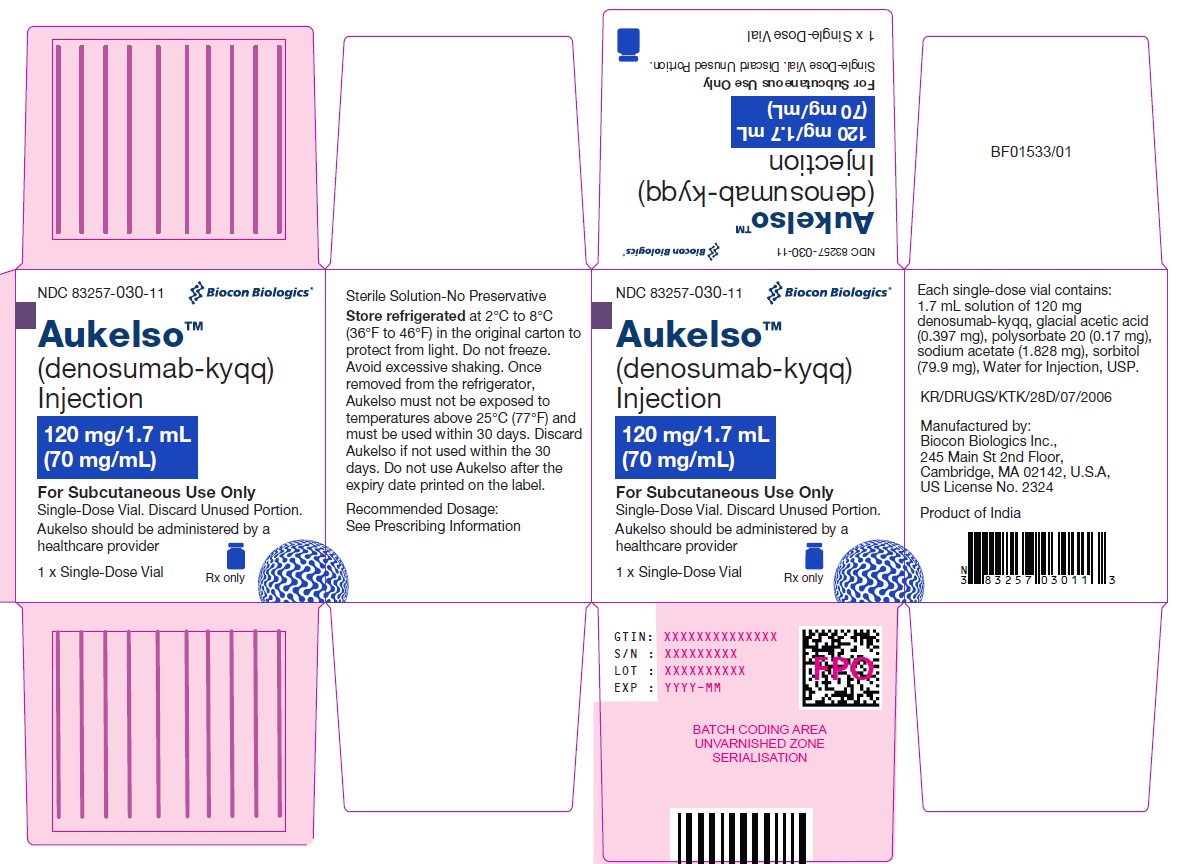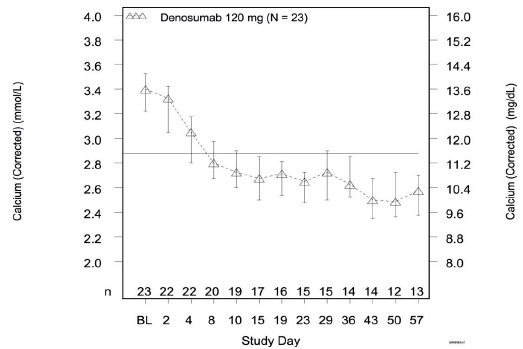 DRUG LABEL: AUKELSO
NDC: 83257-030 | Form: INJECTION
Manufacturer: Biocon Biologics Inc.
Category: prescription | Type: HUMAN PRESCRIPTION DRUG LABEL
Date: 20250916

ACTIVE INGREDIENTS: DENOSUMAB 120 mg/1.7 mL
INACTIVE INGREDIENTS: ACETIC ACID 0.397 mg/1.7 mL; SODIUM ACETATE 1.828 mg/1.7 mL; POLYSORBATE 20 0.17 mg/1.7 mL; SORBITOL 79.9 mg/1.7 mL; WATER

HIGHLIGHTS OF PRESCRIBING INFORMATION

These highlights do not include all the information needed to use AUKELSO safely and effectively. See full prescribing information for AUKELSO.
AUKELSOTM (denosumab-kyqq) injection, for subcutaneous use
Initial U.S. Approval: 2025
AUKELSOTM (denosumab-kyqq) is biosimilar* to XGEVA® (denosumab).

1 INDICATIONS AND USAGE

Aukelso is a RANK ligand (RANKL) inhibitor indicated for:

- Prevention of skeletal-related events in patients with multiple myeloma and in patients with bone metastases from solid tumors. (1.1)
- Treatment of adults and skeletally mature adolescents with giant cell tumor of bone that is unresectable or where surgical resection is likely to result in severe morbidity. (1.2, 14.3)
- Treatment of hypercalcemia of malignancy refractory to bisphosphonate therapy. (1.3)

2 DOSAGE AND ADMINISTRATION

- Aukelso should be administered by a healthcare provider. (2.1)
- Aukelso is intended for subcutaneous route only and should not be administered intravenously, intramuscularly, or intradermally. (2.1)
- Multiple Myeloma and Bone Metastasis from Solid Tumors: Administer 120 mg every 4 weeks as a subcutaneous injection in the upper arm, upper thigh, or abdomen. (2.2)
- Giant Cell Tumor of Bone: Administer 120 mg every 4 weeks with additional 120 mg doses on Days 8 and 15 of the first month of therapy. Administer subcutaneously in the upper arm, upper thigh, or abdomen. (2.3)
- Administer calcium and vitamin D as necessary to treat or prevent hypocalcemia. (2.2, 2.3)
- Hypercalcemia of Malignancy: Administer 120 mg every 4 weeks with additional 120 mg doses on Days 8 and 15 of the first month of therapy. Administer subcutaneously in the upper arm, upper thigh, or abdomen. (2.4)

3 DOSAGE FORMS AND STRENGTHS

- Injection: 120 mg/1.7 mL (70 mg/mL) solution in a single-dose vial (3)

4 CONTRAINDICATIONS

- Hypocalcemia (4.1)
- Known clinically significant hypersensitivity to denosumab products (4.2)

5 WARNINGS AND PRECAUTIONS

- Drug Products with Same Active Ingredient: Patients receiving Aukelso should not receive other denosumab products concomitantly. (5.1)
- Hypersensitivity reactions including anaphylaxis may occur. Discontinue permanently if a clinically significant reaction occurs. (5.2)
- Hypocalcemia: Denosumab products can cause severe symptomatic hypocalcemia, Fatal cases have been reported with denosumab products use. Correct hypocalcemia prior to initiating Aukelso. Monitor calcium levels during therapy, especially in the first weeks of initiating therapy, and adequately supplement all patients with calcium and vitamin D. (5.3)
- Osteonecrosis of the jaw (ONJ) has been reported in patients receiving denosumab products. Perform an oral examination prior to starting Aukelso. Monitor for symptoms. Avoid invasive dental procedures during treatment with Aukelso. (5.4)
- Atypical femoral fracture: Evaluate patients with thigh or groin pain to rule out a femoral fracture. (5.5)
- Hypercalcemia Following Treatment Discontinuation in Patients with Giant Cell Tumor of Bone and in Patients with Growing Skeletons: Monitor patients for signs and symptoms of hypercalcemia, and manage as clinically appropriate. (5.6, 8.4)
- Multiple Vertebral Fractures (MVF) Following Treatment Discontinuation: When Aukelso treatment is discontinued, evaluate the individual patient’s risk for vertebral fractures. (5.7)
- Embryo-Fetal Toxicity: Can cause fetal harm. Advise females of reproductive potential of potential risk to the fetus and to use effective contraception. (5.8, 8.1, 8.3)

6 ADVERSE REACTIONS

- Bone Metastasis from Solid Tumors: Most common adverse reactions (≥ 25%) were fatigue/asthenia, hypophosphatemia, and nausea. (6.1)
- Multiple Myeloma: Most common adverse reactions (≥ 10%) were diarrhea, nausea, anemia, back pain, thrombocytopenia, peripheral edema, hypocalcemia, upper respiratory tract infection, rash, and headache. (6.1)
- Giant Cell Tumor of Bone: Most common adverse reactions (≥ 10%) were arthralgia, headache, nausea, back pain, fatigue, and pain in extremity. (6.1)
- Hypercalcemia of Malignancy: Most common adverse reactions (> 20%) were nausea, dyspnea, decreased appetite, headache, peripheral edema, vomiting, anemia, constipation, and diarrhea. (6.1)

To report SUSPECTED ADVERSE REACTIONS, contact Biocon Biologics at 1-833-986-1468 or FDA at 1-800-FDA-1088 or www.fda.gov/medwatch.

8 USE IN SPECIFIC POPULATIONS

- Pediatric patients: Recommended only for treatment of skeletally mature adolescents with giant cell tumor of bone. (8.4)
- Renal impairment: Patients with creatinine clearance less than 30 mL/min or receiving dialysis are at risk for hypocalcemia. Adequately supplement with calcium and vitamin D. (8.6)

* Biosimilar means that the biological product is approved based on data demonstrating that it is highly similar to an FDA-approved biological product, known as a reference product, and that there are no clinically meaningful differences between the biosimilar product and the reference product. Biosimilarity of Aukelso has been demonstrated for the condition(s) of use (e.g., indication(s), dosing regimen(s)), strength(s), dosage form(s), and route(s) of administration described in its Full Prescribing Information

FULL PRESCRIBING INFORMATION

1 INDICATIONS AND USAGE

1.1 Multiple Myeloma and Bone Metastasis from Solid Tumors

Aukelso is indicated for the prevention of skeletal-related events in patients with multiple myeloma and in patients with bone metastases from solid tumors.

1.2 Giant Cell Tumor of Bone

Aukelso is indicated for the treatment of adults and skeletally mature adolescents with giant cell tumor of bone that is unresectable or where surgical resection is likely to result in severe morbidity [see Clinical Trials (14.2)].

1.3 Hypercalcemia of Malignancy

Aukelso is indicated for the treatment of hypercalcemia of malignancy refractory to bisphosphonate therapy.

2 DOSAGE AND ADMINISTRATION

2.1 Important Administration Instructions

Aukelso should be administered by a healthcare provider.

Aukelso is intended for subcutaneous route only and should not be administered intravenously, intramuscularly, or intradermally.

2.2 Multiple Myeloma and Bone Metastasis from Solid Tumors

The recommended dose of Aukelso is 120 mg administered as a subcutaneous injection every 4 weeks in the upper arm, upper thigh, or abdomen.

Administer calcium and vitamin D as necessary to treat or prevent hypocalcemia [see Warnings and Precautions (5.3)].

2.3 Giant Cell Tumor of Bone

The recommended dose of Aukelso is 120 mg administered every 4 weeks with additional 120 mg doses on Days 8 and 15 of the first month of therapy. Administer subcutaneously in the upper arm, upper thigh, or abdomen.

Administer calcium and vitamin D as necessary to treat or prevent hypocalcemia [see Warnings and Precautions (5.3)].

2.4 Hypercalcemia of Malignancy

The recommended dose of Aukelso is 120 mg administered every 4 weeks with additional 120 mg doses on Days 8 and 15 of the first month of therapy. Administer subcutaneously in the upper arm, upper thigh, or abdomen.

2.5 Preparation and Administration

Parenteral drug products should be inspected visually for particulate matter and discoloration prior to administration whenever solution and container permit. Aukelso is a clear to slightly opalescent, colorless to pale yellow solution. Do not use if the solution is discolored or cloudy or if the solution contains visible particles or foreign particulate matter.

Prior to administration, Aukelso may be removed from the refrigerator and brought to room temperature up to 25°C (77°F) by standing in the original container. This generally takes 15 to 30 minutes. Do not warm Aukelso in any other way [see How Supplied/Storage and Handling (16)].

Use a 27-gauge needle to withdraw and inject the entire contents of the vial. Do not re-enter the vial. Discard vial after single entry.

3 DOSAGE FORMS AND STRENGTHS

Injection: 120 mg/1.7 mL (70 mg/mL) clear to slightly opalescent, colorless to pale yellow solution in a single-dose vial

4 CONTRAINDICATIONS

4.1 Hypocalcemia

Pre-existing hypocalcemia must be corrected prior to initiating therapy with Aukelso [see Warnings and Precautions (5.3)].

4.2 Hypersensitivity

Aukelso is contraindicated in patients with known clinically significant hypersensitivity to denosumab products [see Warnings and Precautions (5.2) and Adverse Reactions (6.2)].

5 WARNINGS AND PRECAUTIONS

5.1 Drug Products with Same Active Ingredient

Patients receiving Aukelso should not receive other denosumab products concomitantly.

5.2 Hypersensitivity

Clinically significant hypersensitivity including anaphylaxis has been reported with use of denosumab products. Reactions may include hypotension, dyspnea, upper airway edema, lip swelling, rash, pruritus, and urticaria. If an anaphylactic or other clinically significant allergic reaction occurs, initiate appropriate therapy and discontinue Aukelso therapy permanently [see Contraindications (4.2) and Adverse Reactions (6.2)].

5.3 Hypocalcemia

Denosumab products can cause severe symptomatic hypocalcemia, and fatal cases have been reported. Correct pre-existing hypocalcemia prior to Aukelso treatment. Monitor calcium levels, throughout Aukelso therapy, especially in the first weeks of initiating therapy, and administer calcium, magnesium, and vitamin D as necessary. Concomitant use of calcimimetics and other drugs that can lower calcium levels may worsen hypocalcemia risk and serum calcium should be closely monitored. Advise patients to contact a healthcare provider for symptoms of hypocalcemia [see Contraindications (4.1), Adverse Reactions (6.1, 6.2), and Patient Counseling Information (17)].

An increased risk of hypocalcemia has been observed in clinical trials of patients with increasing renal dysfunction, most commonly with severe dysfunction (creatinine clearance less than 30 mL/min and/or on dialysis), and with inadequate/no calcium supplementation. Monitor calcium levels and calcium and vitamin D intake [see Adverse Reactions (6.1), Use in Specific Populations (8.6), and Clinical Pharmacology (12.3)].

5.4 Osteonecrosis of the Jaw (ONJ)

Osteonecrosis of the jaw (ONJ) has been reported in patients receiving denosumab products, manifesting as jaw pain, osteomyelitis, osteitis, bone erosion, tooth or periodontal infection, toothache, gingival ulceration, or gingival erosion. Persistent pain or slow healing of the mouth or jaw after dental surgery may also be manifestations of ONJ. In clinical trials in patients with cancer, the incidence of ONJ was higher with longer duration of exposure [see Adverse Reactions (6.1)]. Seventy-nine percent of patients with ONJ had a history of tooth extraction, poor oral hygiene, or use of a dental appliance as a predisposing factor.

Other risk factors for the development of ONJ include immunosuppressive therapy, treatment with angiogenesis inhibitors, systemic corticosteroids, diabetes, and gingival infections. Similarly, for denosumab-treated patients with multiple myeloma that developed ONJ, 58% had a history of invasive dental procedures as a predisposing factor.

Perform an oral examination and appropriate preventive dentistry prior to the initiation of Aukelso and periodically during Aukelso therapy. Advise patients regarding oral hygiene practices. Avoid invasive dental procedures during treatment with Aukelso. Consider temporary discontinuation of Aukelso therapy if an invasive dental procedure must be performed. There are no data available to suggest the optimal duration of treatment interruption.

Patients who are suspected of having or who develop ONJ while on Aukelso should receive care by a dentist or an oral surgeon. In these patients, extensive dental surgery to treat ONJ may exacerbate the condition. Clinical judgment of the treating healthcare provider should guide the management plan of each patient based on individual risk/benefit assessment.

5.5 Atypical Subtrochanteric and Diaphyseal Femoral Fracture

Atypical femoral fracture has been reported with denosumab products [see Adverse Reactions (6.1)]. These fractures can occur anywhere in the femoral shaft from just below the lesser trochanter to above the supracondylar flare and are transverse or short oblique in orientation without evidence of comminution.

Atypical femoral fractures most commonly occur with minimal or no trauma to the affected area. They may be bilateral and many patients report prodromal pain in the affected area, usually presenting as dull, aching thigh pain, weeks to months before a complete fracture occurs. A number of reports note that patients were also receiving treatment with glucocorticoids (e.g. prednisone) at the time of fracture.

During Aukelso treatment, patients should be advised to report new or unusual thigh, hip, or groin pain. Any patient who presents with thigh or groin pain should be suspected of having an atypical fracture and should be evaluated to rule out an incomplete femur fracture. Patient presenting with an atypical femur fracture should also be assessed for symptoms and signs of fracture in the contralateral limb. Interruption of Aukelso therapy should be considered, pending a risk/benefit assessment, on an individual basis.

5.6 Hypercalcemia Following Treatment Discontinuation in Patients with Giant Cell Tumor of Bone and in Patients with Growing Skeletons

Clinically significant hypercalcemia requiring hospitalization and complicated by acute renal injury has been reported in denosumab product-treated patients with giant cell tumor of bone and patients with growing skeletons. Hypercalcemia has been reported within the first year after treatment discontinuation. After treatment is discontinued, monitor patients for signs and symptoms of hypercalcemia, assess serum calcium periodically, reevaluate the patient’s calcium and vitamin D supplementation requirements and manage patients as clinically appropriate [see Adverse Reactions (6) and Use in Specific Populations (8.4)].

5.7 Multiple Vertebral Fractures (MVF) Following Treatment Discontinuation

Multiple vertebral fractures (MVF) have been reported following discontinuation of treatment with denosumab products. Patients at higher risk for MVF include those with risk factors for or a history of osteoporosis or prior fractures.

When Aukelso treatment is discontinued, evaluate the individual patient’s risk for vertebral fractures [see Patient Counseling Information (17)].

5.8 Embryo-Fetal Toxicity

Based on data from animal studies and its mechanism of action, denosumab products can cause fetal harm when administered to a pregnant woman. In animal reproduction studies, administration of denosumab to cynomolgus monkeys throughout pregnancy at a dose 25-fold higher than the recommended human dose of denosumab based on body weight resulted in increased fetal loss, stillbirths, and postnatal mortality, along with evidence of absent peripheral lymph nodes, abnormal bone growth and decreased neonatal growth.

Verify the pregnancy status of females of reproductive potential prior to the initiation of Aukelso. Advise pregnant women and females of reproductive potential that exposure to Aukelso during pregnancy or within 5 months prior to conception can result in fetal harm. Advise females of reproductive potential to use effective contraception during therapy, and for at least 5 months after the last dose of Aukelso [see Use in Specific Populations (8.1, 8.3) and Clinical Pharmacology (12.1)].

6 ADVERSE REACTIONS

The following adverse reactions are discussed below and elsewhere in the labeling:

- Hypersensitivity [see Warnings and Precautions (5.2)]
- Hypocalcemia [see Warnings and Precautions (5.3) and Use in Specific Populations (8.6)]
- Osteonecrosis of the Jaw [see Warnings and Precautions (5.4)]
- Atypical Subtrochanteric and Diaphyseal Femoral Fracture [see Warnings and Precautions (5.5)]
- Hypercalcemia following treatment discontinuation in patients with giant cell tumor of bone and in patients with growing skeletons [see Warnings and Precautions (5.6) and Use in Specific Populations (8.4)]
- Multiple vertebral fractures (MVF) following treatment discontinuation [see Warnings and Precautions (5.7)]

6.1 Clinical Trials Experience

Because clinical trials are conducted under widely varying conditions, adverse reaction rates observed in the clinical trials of a drug cannot be directly compared to rates in the clinical trials of another drug and may not reflect the rates observed in practice.

Bone Metastasis from Solid Tumors

The safety of denosumab was evaluated in three randomized, double-blind, double-dummy trials [see Clinical Trials (14.1)] in which a total of 2841 patients with bone metastasis from prostate cancer, breast cancer, or other solid tumors, or lytic bony lesions from multiple myeloma received at least one dose of denosumab. In Studies 20050136, 20050244, and 20050103, patients were randomized to receive either 120 mg of denosumab every 4 weeks as a subcutaneous injection or 4 mg (dose adjusted for reduced renal function) of zoledronic acid every 4 weeks by intravenous (IV) infusion. Entry criteria included serum calcium (corrected) from 8 to 11.5 mg/dL (2 to 2.9 mmol/L) and creatinine clearance 30 mL/min or greater.

Patients who had received IV bisphosphonates were excluded, as were patients with prior history of ONJ or osteomyelitis of the jaw, an active dental or jaw condition requiring oral surgery, non-healed dental/oral surgery, or any planned invasive dental procedure. During the study, serum chemistries including calcium and phosphorus were monitored every 4 weeks. Calcium and vitamin D supplementation was recommended but not required.

The median duration of exposure to denosumab was 12 months (range: 0.1-41) and median duration on-study was 13 months (range: 0.1-41). Of patients who received denosumab, 46% were female. Eighty-five percent were White, 5% Hispanic/Latino, 6% Asian, and 3% Black. The median age was 63 years (range: 18-93). Seventy-five percent of patients who received denosumab received concomitant chemotherapy.

The most common adverse reactions in patients (incidence greater than or equal to 25%) were fatigue/asthenia, hypophosphatemia, and nausea (see Table 1). The most common serious adverse reaction was dyspnea. The most common adverse reactions resulting in discontinuation of denosumab were osteonecrosis and hypocalcemia.

Table 1. Selecteda Adverse Reactions of Any Severity (Studies 20050136, 20050244, and 20050103)

Body System | Denosumab; n = 2841; % | Zoledronic Acid; n = 2836; %
GASTROINTESTINAL
Nausea | 31 | 32
Diarrhea | 20 | 19
GENERAL
Fatigue/Asthenia | 45 | 46
INVESTIGATIONS
Hypocalcemiab | 18 | 9
Hypophosphatemiab | 32 | 20
NEUROLOGICAL
Headache | 13 | 14
RESPIRATORY
Dyspnea | 21 | 18
Cough | 15 | 15

aAdverse reactions reported in at least 10% of patients receiving denosumab in Studies 20050136, 20050244, and 20050103, and meeting one of the following criteria:

- At least 1% greater incidence in denosumab-treated patients, or
- Between-group difference (either direction) of less than 1% and more than 5% greater incidence in patients treated with zoledronic acid compared to placebo (US Prescribing Information for zoledronic acid)

bLaboratory-derived and below the central laboratory lower limit of normal [8.3 - 8.5 mg/dL (2.075 - 2.125 mmol/L) for calcium and 2.2 - 2.8 mg/dL (0.71 - 0.9 mmol/L) for phosphorus]

Severe Mineral/Electrolyte Abnormalities

- Severe hypocalcemia (corrected serum calcium less than 7 mg/dL or less than 1.75 mmol/L) occurred in 3.1% of patients treated with denosumab and 1.3% of patients treated with zoledronic acid. Of patients who experienced severe hypocalcemia, 33% experienced 2 or more episodes of severe hypocalcemia and 16% experienced 3 or more episodes [see Warnings and Precautions (5.3) and Use in Specific Populations (8.6)].
- Severe hypophosphatemia (serum phosphorus less than 2 mg/dL or less than 0.6 mmol/L) occurred in 15% of patients treated with denosumab and 7% of patients treated with zoledronic acid.

Osteonecrosis of the Jaw (ONJ)

In the primary treatment phases of Studies 20050136, 20050244, and 20050103, ONJ was confirmed in 1.8% of patients in the denosumab group (median exposure of 12.0 months; range: 0.1-41) and 1.3% of patients in the zoledronic acid group. The trials in patients with breast (Study 20050136) or prostate (Study 20050103) cancer included an open-label extension treatment phase where patients were offered denosumab 120 mg once every 4 weeks (median overall exposure of 14.9 months; range: 0.1-67.2). The patient-year adjusted incidence (number of events per 100 patient years) of confirmed ONJ was 1.1% during the first year of treatment, 3.7% in the second year, and 4.6% per year thereafter. The median time to ONJ was 20.6 months (range: 4-53) [see Warnings and Precautions (5.4)].

In a placebo-controlled clinical trial with an extension treatment phase evaluating denosumab for the prevention of bone metastases in patients with non-metastatic prostate cancer (a patient population for which denosumab is not indicated), with longer treatment exposure of up to 7 years, the patient-year adjusted incidence (number of events per 100 patient years) of confirmed ONJ was 1.1% during the first year of treatment, 3% in the second year, and 7% per year thereafter.

Atypical Subtrochanteric and Diaphyseal Fracture

In the clinical trial program, atypical femoral fracture has been reported in patients treated with denosumab and the risk increased with longer duration of treatment. Events have occurred during treatment and after treatment was discontinued [see Warnings and Precautions (5.5)].

Multiple Myeloma

The safety of denosumab was evaluated in an international, randomized (1:1), double-blind, active-controlled trial of patients with newly diagnosed multiple myeloma with treatment through disease progression [see Clinical Trials (14.2)]. In this trial, patients received 120 mg denosumab every 4 weeks as a subcutaneous injection (n = 850) or 4 mg (dose adjusted for renal function) of zoledronic acid intravenously (IV) every 4 weeks by IV infusion (n = 852). Entry criteria included serum calcium (corrected) from 8 to 11.5 mg/dL (2 to 2.9 mmol/L) and creatinine clearance 30 mL/min or greater. Patients who had received IV bisphosphonates were excluded, as were patients with prior history of ONJ or osteomyelitis of the jaw, an active dental or jaw condition requiring oral surgery, non-healed dental/oral surgery, or any planned invasive dental procedure. During the study, serum chemistries including calcium and phosphorus were monitored every 4 weeks. Calcium and vitamin D supplementation was recommended but not required.

The median duration of exposure to denosumab was 16 months (range: 1-50) and median duration on-study was 17 months (range: 0-49). Of patients who received denosumab, 46% were female, 83% percent were White, 13% Asian, 3% Black or African American, and 4% Hispanic/Latino. The median age of the patients randomized to denosumab was 63 years (range: 29-91) and all patients who received denosumab received concomitant anti-myeloma chemotherapy.

The adverse reaction profile of denosumab in patients with multiple myeloma, Study 20090482, was similar to that observed in Studies 20050136, 20050244, and 20050103. The most common adverse reactions (incidence ≥ 10%) were diarrhea (34%), nausea (32%), anemia (22%), back pain (21%), thrombocytopenia (19%), peripheral edema (17%), hypocalcemia (16%), upper respiratory tract infection (15%), rash (14%), and headache (11%). The most common serious adverse reaction (incidence ≥ 5%) was pneumonia (8%). The most common adverse reaction resulting in discontinuation of denosumab (≥ 1%) was osteonecrosis of the jaw.

Hypocalcemia and Hypophosphatemia

Severe hypocalcemia (corrected serum calcium less than 7 mg/dL or less than 1.75 mmol/L) and severe hypophosphatemia (serum phosphorus less than 2 mg/dL or less than 0.6 mmol/L) occurred in 2% and 21% patients treated with denosumab, respectively.

Osteonecrosis of the Jaw (ONJ)

In the primary treatment phase of Study 20090482, ONJ was confirmed in 4.1% of patients in the denosumab group (median exposure of 16 months; range: 1-50) and 2.8% of patients in the zoledronic acid group (median 15 months, range: 1-45 months). At the completion of the double-blind treatment phase of Study 20090482, the patient-year adjusted incidence (number of events per 100 patient years) of confirmed ONJ in the denosumab group (median exposure of 19.4 months; rang: 1-52) was 2% during the first year of treatment, 5% in the second year, and 4.5% per year thereafter. The median time to ONJ was 18.7 months (range: 1-44) [see Warnings and Precautions (5.4)].

Giant Cell Tumor of Bone

The safety of denosumab was evaluated in two single-arm trials (Study 20062004 and Study 20040215) [see Clinical Trials (14.3)] in which a total of 548 adult or skeletally mature adolescent patients with giant cell tumor of bone received at least 1 dose of denosumab. Patients received 120 mg denosumab subcutaneously every 4 weeks with additional 120 mg doses on Days 8 and 15 of the first month of therapy. Patients receiving concurrent bisphosphonate therapy were excluded from enrollment in both studies. Patients with prior history of ONJ or osteomyelitis of the jaw, an active dental or jaw condition requiring oral surgery, non-healed dental/oral surgery, or any planned invasive dental procedure were excluded from enrollment in Study 20040215. During the trial, serum chemistries including calcium and phosphorus were monitored every 4 weeks. Calcium and vitamin D supplementation was recommended but not required.

Of the 548 patients who received denosumab, 467 patients were treated with denosumab for ≥ 1 year, 323 patients for ≥ 2 years, and 255 patients for ≥ 3 years. The median number of doses received was 33 (range: 4 -138 doses) and the median number of months on-study was 60 (range: 0-140 months). Fifty-seven percent of the enrolled patients were women and 82% were White. The median age was 33 years (range: 13-83 years); a total of 19 patients were skeletally mature adolescents (12 to ˂17 years of age).

The common adverse reaction profile of denosumab in patients with giant cell tumor of bone was generally similar to that reported in Studies 20050136, 20050244, and 20050103. The most common adverse reactions in patients (incidence ≥ 10%) were arthralgia, back pain, pain in extremity, fatigue, headache, nausea, nasopharyngitis, musculoskeletal pain, toothache, vomiting, hypophosphatemia, constipation, diarrhea, and cough. The most frequent serious adverse reactions were osteonecrosis of the jaw (3.6%), bone giant cell tumor (1.5%), anemia (1.1%), pneumonia (0.9%), and back pain (0.9%). The most frequent adverse reactions resulting in discontinuation of denosumab was osteonecrosis of the jaw (incidence of 3.6%). The adverse reaction profile appeared similar in skeletally mature adolescents and adults.

Hypocalcemia and Hypophosphatemia

- Moderate to severe hypocalcemia (corrected serum calcium less than 8 mg/dL or less than 2 mmol/L) occurred in 5% of patients treated with denosumab.
- Severe hypophosphatemia (serum phosphorus less than 2 to 1 mg/dL or less than 0.6 to 0.3 mmol/L) occurred in 20% of patients treated with denosumab.

Osteonecrosis of the Jaw (ONJ)

In the pooled analysis of Study 20062004 and Study 20040215, ONJ was confirmed in 7% of patients who received denosumab (median number of doses received: 33; range: 4-138 doses).

Study 20140114 (NCT03301857) was a 5-year long term follow-up study for patients (n = 85) who completed Study 20062004. In Study 20062004 and Study 20140114 combined, ONJ was confirmed in 7% of patients who received denosumab (median time on trial 62.2 months (range 0 - 173). The combined patient-year adjusted incidence (number of events per 100 patient years) of confirmed ONJ was 0.2% during the first year of treatment, 1.5% in the second year, 1.8% in the third year, 2.1% in the fourth year, 1.4% in the fifth year, and 1.5% thereafter. [see Warnings and Precautions (5.4)].

Atypical Subtrochanteric and Diaphyseal Fracture

In the pooled analysis of Study 20062004 and Study 20040215, atypical femoral fracture was observed in 0.9% of patients who received denosumab (median number of doses received: 33; range: 4-138 doses).

In Study 20062004 and Study 20140114, the combined incidence of confirmed atypical femoral fracture was 1.3% of patients who received denosumab [see Warnings and Precautions (5.5)].

Hypercalcemia Following Treatment Discontinuation

In the pooled safety population, 0.7% of patients experienced serious adverse events of hypercalcemia > 30 days following treatment discontinuation that was recurrent in some patients [see Warnings and Precautions (5.6)].

Hypercalcemia of Malignancy

Denosumab was evaluated in an open-label, single-arm trial (Study 20070315) in which 33 patients with hypercalcemia of malignancy (with or without bone metastases) refractory to treatment with intravenous bisphosphonate therapy were enrolled [see Clinical Trials (14.4)].

The adverse reaction profile of denosumab in patients with hypercalcemia of malignancy was similar to that reported in Studies 20050136, 20050244, 20050103, 20062004, and 20040215. Adverse reactions occurring in greater than 20% of patients were nausea (30%), dyspnea (27%), decreased appetite (24%), headache (24%), peripheral edema (24%), vomiting (24%), anemia (21%), constipation (21%), and diarrhea (21%). The following adverse reactions of Grade 3 or greater severity related to study therapy were reported on-study: fatigue (3%) and infection (6%). Grade 3 laboratory abnormalities included hypomagnesemia (3%), hypokalemia (3%), and hypophosphatemia (76%) of patients. No deaths on-study were related to denosumab therapy.

6.2 Postmarketing Experience

The following adverse reactions have been identified during post approval use of denosumab products. Because these reactions are reported voluntarily from a population of uncertain size, it is not always possible to reliably estimate their frequency or establish a causal relationship to drug exposure.

- Hypocalcemia: Severe symptomatic hypocalcemia, including fatal cases [see Contraindications (4.1) and Warnings and Precautions (5.3)].
- Hypercalcemia: Severe symptomatic hypercalcemia following treatment discontinuation can occur [see Adverse Reactions (6) and Warnings and Precautions (5.6)].
- Hypersensitivity, including anaphylactic reactions [see Contraindications (4.2) and Warnings and Precautions (5.2)].
- Musculoskeletal pain, including severe musculoskeletal pain. Positive re-challenge has been reported.
- Lichenoid drug eruptions (e.g., lichen planus-like reactions).
- Alopecia.

8 USE IN SPECIFIC POPULATIONS

8.1 Pregnancy

Risk Summary

Based on findings in animals and its mechanism of action, denosumab products can cause fetal harm when administered to a pregnant woman [see Clinical Pharmacology (12.1)]. There are insufficient data with denosumab products use in pregnant women to inform any drug associated risks for adverse developmental outcomes. In utero denosumab exposure from cynomolgus monkeys dosed monthly with denosumab throughout pregnancy at a dose 25-fold higher than the recommended human dose of denosumab based on body weight resulted in increased fetal loss, stillbirths, and postnatal mortality; and absent lymph nodes, abnormal bone growth, and decreased neonatal growth [see Data].

Apprise pregnant women of the potential risk to the fetus.

The background rate of major birth defects and miscarriage is unknown for the indicated population. In the U.S. general population, the estimated background risk of major birth defects and miscarriage in clinically recognized pregnancies is 2-4% and 15-20%, respectively.

Data

Animal Data

The effects of denosumab on prenatal development have been studied in both cynomolgus monkeys and genetically engineered mice in which RANK ligand (RANKL) expression was turned off by gene removal (a “knockout mouse”). In cynomolgus monkeys dosed subcutaneously with denosumab throughout pregnancy starting at gestational day 20 and at a pharmacologically active dose 25-fold higher than the recommended human dose of denosumab based on body weight, there was increased fetal loss during gestation, stillbirths, and postnatal mortality. Other findings in offspring included absence of axillary, inguinal, mandibular, and mesenteric lymph nodes; abnormal bone growth, reduced bone strength, reduced hematopoiesis, dental dysplasia, and tooth malalignment; and decreased neonatal growth. At birth out to one month of age, infants had measurable blood levels of denosumab (22-621% of maternal levels).

Following a recovery period from birth out to 6 months of age, the effects on bone quality and strength returned to normal; there were no adverse effects on tooth eruption, though dental dysplasia was still apparent; axillary and inguinal lymph nodes remained absent, while mandibular and mesenteric lymph nodes were present, though small; and minimal to moderate mineralization in multiple tissues was seen in one recovery animal. There was no evidence of maternal harm prior to labor; adverse maternal effects occurred infrequently during labor. Maternal mammary gland development was normal. There was no fetal NOAEL (no observable adverse effect level) established for this study because only one dose of 50 mg/kg was evaluated. Mammary gland histopathology at 6 months of age was normal in female offspring exposed to denosumab in utero; however, development and lactation have not been fully evaluated.

In RANKL knockout mice, absence of RANKL (the target of denosumab) also caused fetal lymph node agenesis and led to postnatal impairment of dentition and bone growth. Pregnant RANKL knockout mice showed altered maturation of the maternal mammary gland, leading to impaired lactation [see Use in Specific Populations (8.3) and Nonclinical Toxicology (13.2)].

8.2 Lactation

Risk Summary

There is no information regarding the presence of denosumab products in human milk, the effects on the breastfed child, or the effects on milk production. Denosumab was detected in the maternal milk of cynomolgus monkeys up to 1 month after the last dose of denosumab (≤ 0.5% milk:serum ratio) and maternal mammary gland development was normal, with no impaired lactation. However, pregnant RANKL knockout mice showed altered maturation of the maternal mammary gland, leading to impaired lactation [see Use in Specific Populations (8.1) and Nonclinical Toxicology (13.2)]. Consider the developmental and health benefits of breastfeeding along with the mother’s clinical need for Aukelso treatment and any potential adverse effects on the breastfed child from Aukelso or from the underlying maternal condition.

8.3 Females and Males of Reproductive Potential

Based on findings in animals and its mechanism of action, denosumab products can cause fetal harm when administered to a pregnant woman [see Use in Specific Populations (8.1)].

Pregnancy Testing

Verify the pregnancy status of females of reproductive potential prior to initiating Aukelso treatment.

Contraception

Females

Advise females of reproductive potential to use effective contraception during therapy, and for at least 5 months after the last dose of Aukelso.

8.4 Pediatric Use

The safety and efficacy of Aukelso have not been established in pediatric patients except in skeletally mature adolescents (aged 12–16 years) with giant cell tumor of bone. Aukelso is recommended only for treatment of skeletally mature adolescents (aged 12–16 years) with giant cell tumor of bone [see Indications and Usage (1.2)]. Clinically significant hypercalcemia after treatment discontinuation has been reported in pediatric patients with growing skeletons who received denosumab products for giant cell tumor of bone or for unapproved indications [see Adverse Reactions (6.2) and Warnings and Precautions (5.6)].

Denosumab was studied in an open-label trial that enrolled a subset of 19 adolescent patients (aged 12-16 years) with giant cell tumor of bone who had reached skeletal maturity, defined by at least 1 mature long bone (e.g., closed epiphyseal growth plate of the humerus), and had a body weight ≥ 45 kg [see Indications and Usage (1.2) and Clinical Trials (14.3)]. A total of one of five (20%) evaluable adolescent patients had an objective response by retrospective independent assessment of radiographic response according to modified Response Evaluation Criteria in Solid Tumors (RECIST 1.1). The adverse reaction profile and efficacy results appeared to be similar in skeletally mature adolescents and adults [see Adverse Reactions (6.1) and Clinical Trials (14.3)].

Animal Data

Treatment with denosumab products may impair bone growth in children with open growth plates and may inhibit eruption of dentition. In neonatal rats, inhibition of RANKL (the target of denosumab therapy) with a construct of osteoprotegerin bound to Fc (OPG-Fc) at doses ≤ 10 mg/kg was associated with inhibition of bone growth and tooth eruption. Adolescent primates treated with denosumab at doses 5 and 25 times (10 and 50 mg/kg dose) higher than the recommended human dose of 120 mg administered once every 4 weeks, based on body weight (mg/kg), had abnormal growth plates, considered to be consistent with the pharmacological activity of denosumab.

Cynomolgus monkeys exposed in utero to denosumab exhibited bone abnormalities, reduced hematopoiesis, tooth malalignment, decreased neonatal growth, and an absence of axillary, inguinal, mandibular, and mesenteric lymph nodes. Some bone abnormalities recovered once exposure was ceased following birth; however, axillary and inguinal lymph nodes remained absent 6 months post-birth [see Use in Specific Populations (8.1)].

8.5 Geriatric Use

Of the total number of patients in clinical studies that received denosumab (n = 2841) in Studies 20050136, 20050244, and 20050103, 1271 (44%) were ≥ 65 years old, while 473 patients (17%) were ≥ 75 years old. Of the 859 patients in Study 20090482 that received denosumab, 387 patients (45%) were ≥ 65 years old, while 141 patients (16%) were ≥ 75 years old. No overall differences in safety or efficacy were observed between older and younger patients.

8.6 Renal Impairment

Two clinical trials were conducted in patients without cancer and with varying degrees of renal function.

In one study, patients (N = 55) with varying degrees of renal function (ranging from normal through end-stage renal disease requiring dialysis) received a single 60 mg subcutaneous dose of denosumab. In a second study, patients (N = 32) with severe renal dysfunction (creatinine clearance less than 30 mL/min and/or on dialysis) were given two 120 mg subcutaneous doses of denosumab. In both studies, greater risk of developing hypocalcemia was observed with increasing renal impairment, and with inadequate/no calcium supplementation. Hypocalcemia was mild to moderate in severity in 96% of patients. Monitor calcium levels and calcium and vitamin D intake [see Warnings and Precautions (5.3), Adverse Reactions (6.1), and Clinical Pharmacology (12.3)].

10 OVERDOSAGE

There is no experience with overdosage of denosumab products.

11 DESCRIPTION

Denosumab-kyqq is a human IgG2 monoclonal antibody that binds to human RANKL. Denosumab-kyqq has an approximate molecular weight of 147 kDa and is produced in genetically engineered mammalian (Chinese hamster ovary) cells.

Aukelso (denosumab-kyqq) injection is a sterile, preservative-free, clear to slightly opalescent, colorless to pale yellow solution.

Each single-dose vial contains 120 mg denosumab-kyqq, glacial acetic acid (0.397 mg), polysorbate 20 (0.17 mg), sodium acetate (1.828 mg), sorbitol (79.9 mg), Water for Injection (USP), and may contain sodium hydroxide/acetic acid to adjust pH to 5.2.

12 CLINICAL PHARMACOLOGY

12.1 Mechanism of Action

Denosumab products bind to RANKL, a transmembrane or soluble protein essential for the formation, function, and survival of osteoclasts, the cells responsible for bone resorption, thereby modulating calcium release from bone. Increased osteoclast activity, stimulated by RANKL, is a mediator of bone pathology in solid tumors with osseous metastases. Similarly, giant cell tumors of bone consist of stromal cells expressing RANKL and osteoclast-like giant cells expressing RANK receptor, and signaling through the RANK receptor contributes to osteolysis and tumor growth. Denosumab products prevent RANKL from activating its receptor, RANK, on the surface of osteoclasts, their precursors, and osteoclast-like giant cells.

12.2 Pharmacodynamics

In patients with breast cancer and bone metastases, the median reduction in uNTx/Cr was 82% within 1 week following initiation of denosumab 120 mg administered subcutaneously. In Studies 20050136, 20050244, and 20050103, the median reduction in uNTx/Cr from baseline to Month 3 was approximately 80% in 2075 denosumab-treated patients.

In a phase 3 study of patients with newly diagnosed multiple myeloma who received subcutaneous doses of denosumab 120 mg every 4 weeks (Q4W), median reductions in uNTx/Cr of approximately 75% were observed by Week 5. Reductions in bone turnover markers were maintained, with median reductions of 74% to 79% for uNTx/Cr from weeks 9 to 49 of continued 120 mg Q4W dosing.

In adult and skeletally mature adolescent patients with giant cell tumor of bone who received subcutaneous doses of denosumab 120 mg Q4W with a 120 mg loading dose on Days 8 and 15, median reductions in uNTx/Cr from baseline were 84% at Week 13 and 82% at Week 25.

12.3 Pharmacokinetics

Following subcutaneous administration, bioavailability was 62%. Denosumab displayed nonlinear pharmacokinetics at doses below 60 mg, but approximately dose-proportional increases in exposure at higher doses.

With multiple subcutaneous doses of 120 mg once every 4 weeks, up to 2.8-fold accumulation in serum denosumab concentrations was observed and steady-state was achieved by 6 months. A mean (± standard deviation) serum steady-state trough concentration of 20.5 (± 13.5) mcg/mL was achieved by 6 months. The mean elimination half-life was 28 days.

In patients with newly diagnosed multiple myeloma who received 120 mg every 4 weeks, denosumab concentrations appear to reach steady-state by Month 6. In patients with giant cell tumor of bone, after administration of subcutaneous doses of 120 mg once every 4 weeks with additional 120 mg doses on Days 8 and 15 of the first month of therapy, mean (± standard deviation) serum trough concentrations on Day 8, 15, and one month after the first dose were 19.0 (± 24.1), 31.6 (± 27.3), 36.4 (± 20.6) mcg/mL, respectively. Steady-state was achieved in 3 months after initiation of treatment with a mean serum trough concentration of 23.4 (± 12.1) mcg/mL.

Special Populations

Body Weight: A population pharmacokinetic analysis was performed to evaluate the effects of demographic characteristics. Denosumab clearance and volume of distribution were proportional to body weight. The steady-state exposure following repeat subcutaneous administration of 120 mg every 4 weeks to 45 kg and 120 kg subjects were, respectively, 48% higher and 46% lower than exposure of the typical 66 kg subject.

Age, Gender and Race: The pharmacokinetics of denosumab was not affected by age, gender, and race.

Pediatrics: In skeletally-mature adolescent patients (12 to 16 years of age) with giant cell tumor of bone (GCTB) who received 120 mg every 4 weeks with a 120 mg loading dose on Days 8 and 15, the pharmacokinetics of denosumab were comparable to those observed in adult patients with GCTB.

Hepatic Impairment: No clinical trials have been conducted to evaluate the effect of hepatic impairment on the pharmacokinetics of denosumab products.

Renal Impairment: In clinical trials of 87 patients with varying degrees of renal dysfunction, including patients on dialysis, the degree of renal impairment had no effect on the pharmacokinetics and pharmacodynamics of denosumab [see Use in Specific Populations (8.6)].

Drug Interactions

No formal drug-drug interaction trials have been conducted with denosumab. There was no evidence that various anticancer treatments affected denosumab systemic exposure and pharmacodynamic effect. Serum denosumab concentrations at 1 and 3 months and reductions in the bone turnover marker uNTx/Cr (urinary N-terminal telopeptide corrected for creatinine) at 3 months were similar in patients with and without prior intravenous bisphosphonate therapy and were not altered by concomitant chemotherapy and/or hormone therapy.

12.6 Immunogenicity

The observed incidence of anti-drug antibodies is highly dependent on the sensitivity and specificity of the assay. Differences in assay methods preclude meaningful comparisons of the incidence of anti-drug antibodies in the studies described below with the incidence of anti-drug antibodies in other studies, including those of denosumab or of other denosumab products.

Using an electrochemiluminescent bridging immunoassay, less than 1% (55 out of 8113) of patients treated with denosumab for up to 5 years tested positive for binding antibodies (including pre-existing, transient, and developing antibodies). None of the patients tested positive for neutralizing antibodies, as was assessed using a chemiluminescent cell-based in vitro biological assay. There was no identified clinically significant effect of anti-drug antibodies on pharmacokinetics, pharmacodynamics, safety, or effectiveness of denosumab.

13 NONCLINICAL TOXICOLOGY

13.1 Carcinogenesis, Mutagenesis, Impairment of Fertility

Carcinogenicity

The carcinogenic potential of denosumab products has not been evaluated in long-term animal studies.

Mutagenicity

The genotoxic potential of denosumab products has not been evaluated.

Impairment of Fertility

Denosumab had no effect on female fertility or male reproductive organs in monkeys at doses that were 6.5- to 25-fold higher than the recommended human dose of 120 mg subcutaneously administered once every 4 weeks, based on body weight (mg/kg).

13.2 Animal Toxicology and/or Pharmacology

Denosumab products are inhibitors of osteoclastic bone resorption via inhibition of RANKL.

Because the biological activity of denosumab in animals is specific to nonhuman primates, evaluation of genetically engineered (knockout) mice or use of other biological inhibitors of the RANK/RANKL pathway, OPG-Fc and RANK-Fc, provided additional information on the pharmacodynamic properties of denosumab. RANK/RANKL knockout mice exhibited absence of lymph node formation, as well as an absence of lactation due to inhibition of mammary gland maturation (lobulo-alveolar gland development during pregnancy). Neonatal RANK/RANKL knockout mice exhibited reduced bone growth and lack of tooth eruption. A corroborative study in 2-week-old rats given the RANKL inhibitor OPG-Fc also showed reduced bone growth, altered growth plates, and impaired tooth eruption. These changes were partially reversible in this model when dosing with the RANKL inhibitors was discontinued.

14 CLINICAL TRIALS

14.1 Bone Metastasis from Solid Tumors

The safety and efficacy of denosumab for the prevention of skeletal-related events in patients with bone metastases from solid tumors was demonstrated in three international, randomized (1:1), double-blind, active-controlled, noninferiority trials comparing denosumab with zoledronic acid. In all three trials, patients were randomized to receive 120 mg denosumab subcutaneously every 4 weeks or 4 mg zoledronic acid intravenously (IV) every 4 weeks (dose adjusted for reduced renal function). Patients with creatinine clearance less than 30 mL/min were excluded. In each trial, the main outcome measure was demonstration of noninferiority of time to first skeletal-related event (SRE) as compared to zoledronic acid. Supportive outcome measures were superiority of time to first SRE and superiority of time to first and subsequent SRE; testing for these outcome measures occurred if the main outcome measure was statistically significant. An SRE was defined as any of the following: pathologic fracture, radiation therapy to bone, surgery to bone, or spinal cord compression.

Study 20050136 (NCT00321464) enrolled 2046 patients with advanced breast cancer and bone metastasis. Randomization was stratified by a history of prior SRE (yes or no), receipt of chemotherapy within 6 weeks prior to randomization (yes or no), prior oral bisphosphonate use (yes or no), and region (Japan or other countries). Forty percent of patients had a previous SRE, 40% received chemotherapy within 6 weeks prior to randomization, 5% received prior oral bisphosphonates, and 7% were enrolled from Japan. Median age was 57 years, 80% of patients were White, and 99% of patients were women. The median number of doses administered was 18 for denosumab and 17 for zoledronic acid.

Study 20050244 (NCT00330759) enrolled 1776 adults with solid tumors other than breast and castrate-resistant prostate cancer with bone metastasis and multiple myeloma. Randomization was stratified by previous SRE (yes or no), systemic anticancer therapy at time of randomization (yes or no), and tumor type (non-small cell lung cancer, myeloma, or other). Eighty-seven percent were receiving systemic anticancer therapy at the time of randomization, 52% had a previous SRE, 64% of patients were men, 87% were White, and the median age was 60 years. A total of 40% of patients had non-small cell lung cancer, 10% had multiple myeloma, 9% had renal cell carcinoma, and 6% had small cell lung cancer. Other tumor types each comprised less than 5% of the enrolled population. The median number of doses administered was 7 for both denosumab and zoledronic acid.

Study 20050103 (NCT00321620) enrolled 1901 men with castrate-resistant prostate cancer and bone metastasis. Randomization was stratified by previous SRE, PSA level (less than 10 ng/mL or 10 ng/mL or greater) and receipt of chemotherapy within 6 weeks prior to randomization (yes or no). Twenty-six percent of patients had a previous SRE, 15% of patients had PSA less than 10 ng/mL, and 14% received chemotherapy within 6 weeks prior to randomization. Median age was 71 years and 86% of patients were White. The median number of doses administered was 13 for denosumab and 11 for zoledronic acid.

Denosumab delayed the time to first SRE following randomization as compared to zoledronic acid in patients with breast or castrate-resistant prostate cancer (CRPC) with osseous metastases (Table 2). In patients with bone metastasis due to other solid tumors or lytic lesions due to multiple myeloma, denosumab was noninferior to zoledronic acid in delaying the time to first SRE following randomization.

Overall survival and progression-free survival were similar between arms in all three trials.

Table 2. Efficacy Results for Denosumab Compared to Zoledronic Acid

 | Study 20050136 Metastatic Breast Cancer |  | Study 20050244 Metastatic Solid Tumors or Multiple Myeloma |  | Study 20050103 Metastatic CRPCa
 | Denosumab; N = 1026 | Zoledronic Acid; N = 1020 | Denosumab N = 886 | Zoledronic Acid N = 890 | Denosumab N = 950 | Zoledronic Acid N = 951
First On-study SRE
Number of Patients who had SREs (%) | 315 (30.7) | 372 (36.5) | 278 (31.4) | 323 (36.3) | 341 (35.9) | 386 (40.6)
Components of First SRE
Radiation to Bone | 82 (8.0) | 119 (11.7) | 119 (13.4) | 144 (16.2) | 177 (18.6) | 203 (21.3)
Pathological Fracture | 212 (20.7) | 238 (23.3) | 122 (13.8) | 139 (15.6) | 137 (14.4) | 143 (15.0)
Surgery to Bone | 12 (1.2) | 8 (0.8) | 13 (1.5) | 19 (2.1) | 1 (0.1) | 4 (0.4)
Spinal Cord Compression | 9 (0.9) | 7 (0.7) | 24 (2.7) | 21 (2.4) | 26 (2.7) | 36 (3.8)
Median Time to SRE (months) | NRb | 26.4 | 20.5 | 16.3 | 20.7 | 17.1
Hazard Ratio (95% CI) | 0.82 (0.71, 0.95) |  | 0.84 (0.71, 0.98) |  | 0.82 (0.71, 0.95)
Noninferiority p-value | < 0.001 |  | < 0.001 |  | < 0.001
Superiority p-valuec | 0.010 |  | 0.060 |  | 0.008
First and Subsequent SREd
Mean Number/Patient | 0.46 | 0.60 | 0.44 | 0.49 | 0.52 | 0.61
Rate Ratio (95% CI) | 0.77 (0.66, 0.89) |  | 0.90 (0.77, 1.04) |  | 0.82 (0.71, 0.94)
Superiority p-valuee | 0.001 |  | 0.145 |  | 0.009

aCRPC = castrate-resistant prostate cancer.

bNR = not reached.

cSuperiority testing performed only after denosumab demonstrated to be noninferior to zoledronic acid within trial.

dAll skeletal events postrandomization; new events defined by occurrence ≥ 21 days after preceding event.

e Adjusted p-values are presented.

14.2 Multiple Myeloma

The efficacy of denosumab for the prevention of skeletal-related events in newly diagnosed multiple myeloma patients with treatment through disease progression, was evaluated in Study 20090482 (NCT01345019), an international, randomized (1:1), double-blind, active-controlled, noninferiority trial comparing denosumab with zoledronic acid. In this trial, patients were randomized to receive 120 mg denosumab subcutaneously every 4 weeks or 4 mg zoledronic acid intravenously (IV) every 4 weeks (dose adjusted for reduced renal function). Patients with creatinine clearance less than 30 mL/min were excluded. In this trial, the main efficacy outcome measure was noninferiority of time to first skeletal-related event (SRE). Additional efficacy outcome measures were superiority of time to first SRE, time to first and subsequent SRE, and overall survival. An SRE was defined as any of the following: pathologic fracture, radiation therapy to bone, surgery to bone, or spinal cord compression.

Study 20090482 enrolled 1718 newly diagnosed multiple myeloma patients with bone lesions. Randomization was stratified by a history of prior SRE (yes or no), the anti-myeloma agent being utilized/planned to be utilized in first-line therapy (novel therapy-based or non-novel therapy-based [novel therapies include bortezomib, lenalidomide, or thalidomide]), intent to undergo autologous PBSC transplantation (yes or no), stage at diagnosis (International Staging System I or II or III) and region Japan (yes or no). At study enrollment, 96% of the patients were receiving or planning to receive novel therapy-based first-line anti-myeloma therapy, 55% of the patients intended to undergo autologous PBSC transplantation, 61% of patients had a previous SRE, 32% were at ISS Stage I, 38% were at ISS Stage II and 29% were at ISS Stage III, and 2% were enrolled from Japan. Median age was 63 years, 82% of patients were White, and 46% of patients were women. The median number of doses administered was 16 for denosumab and 15 for zoledronic acid.

Denosumab was noninferior to zoledronic acid in delaying the time to first SRE following randomization (HR = 0.98, 95% CI, 0.85-1.14). The results for overall survival (OS) were comparable between denosumab and zoledronic acid treatment groups with a hazard ratio of 0.90 (95% CI: 0.70, 1.16).

Table 3. Efficacy Results for Denosumab Compared to Zoledronic Acid

 | Study 20090482 Multiple Myeloma
 | Denosumab; N = 859 | Zoledronic Acid; N = 859
First On-study SRE
Number of Patients who had SREs (%) | 376 (43.8) | 383 (44.6)
Components of First SRE
Radiation to Bone | 47 (5.5) | 62 (7.2)
Pathological Fracture | 342 (39.8) | 338 (39.3)
Surgery to Bone | 37 (4.3) | 48 (5.6)
Spinal Cord Compression | 6 (0.7) | 4 (0.5)
Median Time to SRE (months) (95% CI) | 22.8; (14.7, NEa) | 24; (16.6, 33.3)
Hazard Ratio (95% CI) | 0.98 (0.85, 1.14)

a NE = not estimable

14.3 Giant Cell Tumor of Bone

The safety and efficacy of denosumab for the treatment of giant cell tumor of bone in adults or skeletally mature adolescents were demonstrated in two open-label trials [Study 20040215 (NCT00396279) and Study 20062004 (NCT00680992)] that enrolled patients with histologically confirmed measurable giant cell tumor of bone that was either recurrent, unresectable, or for which planned surgery was likely to result in severe morbidity. Patients received 120 mg denosumab subcutaneously every 4 weeks with a loading dose on Days 8 and 15 of the first cycle of therapy. Patients who discontinued denosumab then entered the safety follow-up phase for a minimum of 60 months. Retreatment with denosumab while in safety follow-up was allowed for patients who initially demonstrated a response to denosumab (e.g., in the case of recurrent disease).

Study 20040215 was a single-arm, pharmacodynamic, and proof of concept trial conducted in 37 adult patients with unresectable or recurrent giant cell tumor of bone. Patients were required to have histologically confirmed giant cell tumor of bone and radiologic evidence of measurable disease from a computed tomography (CT) or magnetic resonance imaging (MRI) obtained within 28 days prior to study enrollment. Patients enrolled in Study 20040215 underwent CT or MRI assessment of giant cell tumor of bone at baseline and quarterly during denosumab treatment.

Study 20062004 was a parallel-cohort, proof of concept, and safety trial conducted in 535 adult or skeletally mature adolescent patients with histologically confirmed giant cell tumor of bone and evidence of measurable active disease. Study 20062004 enrolled 19 patients who were 12-16 years of age [see Use in Specific Populations (8.4)]. Patients enrolled into one of three cohorts: Cohort 1 enrolled 268 patients with surgically unsalvageable disease (e.g., sacral or spinal sites of disease, or pulmonary metastases); Cohort 2 enrolled 252 patients with surgically salvageable disease where the investigator determined that the planned surgery was likely to result in severe morbidity (e.g., joint resection, limb amputation, or hemipelvectomy); Cohort 3 enrolled 15 patients who previously participated in Study 20040215. Patients underwent imaging assessment of disease status at intervals determined by their treating physician.

A retrospective interim analysis concluded by an independent review committee evaluated objective response in 187 patients enrolled and treated in Study 20040215 and Study 20062004 for whom baseline and at least one post-baseline radiographic assessment were available (27 of 37 patients enrolled in Study 20040215 and 160 of 270 patients enrolled in Cohorts 1 and 2 of Study 20062004). The primary efficacy outcome measure was objective response rate using Response Evaluation Criteria in Solid Tumors (RECIST) v 1.1.

The overall objective response rate (RECIST 1.1) was 25% (95% CI: 19, 32). All responses were partial responses. The estimated median time to response was 3 months. In the 47 patients with an objective response, the median duration of follow-up was 20 months (range: 2-44 months), and 51% (24/47) had a duration of response lasting at least 8 months. Three patients experienced disease progression following an objective response.

14.4 Hypercalcemia of Malignancy

The safety and efficacy of denosumab was demonstrated in an open-label, single-arm trial [Study 20070315 (NCT00896454)] that enrolled 33 patients with hypercalcemia of malignancy (with or without bone metastases) refractory to treatment with intravenous bisphosphonate therapy. Patients received denosumab subcutaneously every 4 weeks with additional 120 mg doses on Days 8 and 15 of the first month of therapy.

In this trial, refractory hypercalcemia of malignancy was defined as an albumin-corrected calcium of > 12.5 mg/dL (3.1 mmol/L) despite treatment with intravenous bisphosphonate therapy in 7-30 days prior to initiation of denosumab therapy. The primary outcome measure was the proportion of patients achieving a response, defined as corrected serum calcium (CSC) ≤ 11.5 mg/dL (2.9 mmol/L), within 10 days after denosumab administration. Efficacy data are summarized in Figure 1 and Table 4. Concurrent chemotherapy did not appear to affect response to denosumab.

Figure 1. Corrected Serum Calcium by Visit in Responders (Median and Interquartile Range)

N = Number of responders who received ≥ 1 dose of investigational product

n = Number of responders who had no missing data at baseline and the time point of interest

Table 4. Efficacy in Patients with Hypercalcemia of Malignancy Refractory to Bisphosphonate Therapy

 | N = 33 | Proportion (%) (95% CI)
All Responders (CSC ≤ 11.5 mg/dL) by Day 10 | 21 | 63.6; (45.1, 79.6)
All Responders by Day 57 | 23 | 69.7; (51.3, 84.4)
Complete Responders (CSC ≤ 10.8 mg/dL) by Day 10 | 12 | 36.4; (20.4, 54.9)
All Complete Responders by Day 57 | 21 | 63.6; (45.1, 79.6)

Median time to response (CSC ≤ 11.5 mg/dL) was 9 days (95% CI: 8, 19), and the median duration of response was 104 days (95% CI: 7, not estimable). Median time to complete response (CSC ≤ 10.8 mg/dL) was 23 days (95% CI: 9, 36), and the median duration of complete response was 34 days (95% CI: 1, 134).

16 HOW SUPPLIED/STORAGE AND HANDLING

Aukelso (denosumab-kyqq) injection is a clear to slightly opalescent, colorless to pale yellow solution supplied in a single-dose vial. The vial stopper is not made with natural rubber latex.

120 mg/1.7 mL (70 mg/mL) | 1 vial per carton | NDC 83257-030-11

Store Aukelso refrigerated at 2°C to 8°C (36°F to 46°F) in the original carton to protect from light. Do not freeze. Prior to administration, Aukelso may be allowed to reach room temperature up to 25°C (77°F) in the original container. Once removed from the refrigerator, Aukelso must not be exposed to temperatures above 25°C (77°F) and must be used within 30 days. Discard Aukelso if not used within the 30 days. Do not use Aukelso after the expiry date printed on the label.

Protect Aukelso from direct light and heat.

Avoid vigorous shaking of Aukelso.

17 PATIENT COUNSELING INFORMATION

Drug Products with Same Active Ingredient

Advise patients that if they receive Aukelso, they should not receive other denosumab products concomitantly [see Warnings and Precautions (5.1)].

Hypersensitivity

Advise patients to seek prompt medical attention if signs or symptoms of hypersensitivity reactions occur. Advise patients who have had signs or symptoms of systemic hypersensitivity reactions that they should not receive denosumab products [see Warnings and Precautions (5.2) and Contraindications (4.2)].

Hypocalcemia

Adequately supplement patients with calcium and vitamin D and instruct them on the importance of maintaining serum calcium levels while receiving Aukelso [see Warnings and Precautions (5.3) and Use in Specific Populations (8.6)]. Advise patients to seek prompt medical attention if they develop signs or symptoms of hypocalcemia.

Osteonecrosis of the Jaw

Advise patients to maintain good oral hygiene during treatment with Aukelso and to inform their dentist prior to dental procedures that they are receiving Aukelso. Patients should avoid invasive dental procedures during treatment with Aukelso and inform their healthcare provider or dentist if they experience persistent pain and/or slow healing of the mouth or jaw after dental surgery [see Warnings and Precautions (5.4)].

Atypical Subtrochanteric and Diaphyseal Femoral Fracture

Advise patients to report new or unusual thigh, hip, or groin pain [see Warnings and Precautions (5.5)].

Hypercalcemia Following Treatment Discontinuation in Patients with Giant Cell Tumor of Bone and in Patients with Growing Skeletons

Advise patients to report nausea, vomiting, headache, and decreased alertness following treatment discontinuation [see Warnings and Precautions (5.6) and Use in Specific Populations (8.4)].

Multiple Vertebral Fractures (MVF) Following Treatment Discontinuation

Advise patients that after treatment with Aukelso is stopped there may be an increased risk of having broken bones in the spine especially in patients who have had a fracture or who have had osteoporosis. Advise patients not to interrupt Aukelso therapy without their physician’s advice [see Warnings and Precautions (5.7)].

Embryo-Fetal Toxicity

Advise females of reproductive potential that Aukelso can cause harm to a fetus and to inform their healthcare provider of a known or suspected pregnancy [see Warnings and Precautions (5.8) and Use in Specific Populations (8.1, 8.3)].

Advise females of reproductive potential to use effective contraception during treatment and for at least 5 months after the last dose of Aukelso [see Use in Specific Populations (8.3)].

AukelsoTM is a trademark of Biocon Biologics Limited.

Copyright © 2025 Biocon Biologics Inc. All rights reserved.

Manufactured by:

Biocon Biologics Inc.

245 Main st, 2nd floor, Cambridge,

MA 02142, U.S.A.

U.S License No. 2324

Product of India

KR/DRUGS/KTK/28D/07/2006

PACKAGE LABEL PRINCIPAL DISPLAY PANEL SECTION

NDC 83257-030-11

AukelsoTM

(denosumab-kyqq)

Injection

120 mg/1.7 mL

(70 mg/mL)

For Subcutaneous Use Only

Single-Dose Vial. Discard Unused Portion.

Aukelso should be administered by a healthcare provider

1 x Single-Dose Vial

Rx only

Each single-dose vial contains: 1.7 mL solution of 120 mg denosumab-kyqq, glacial acetic acid (0.397 mg), polysorbate 20 (0.17 mg), sodium acetate (1.828 mg), sorbitol (79.9 mg), Water for Injection, USP.

Sterile Solution-No Preservative

Store refrigerated at 2°C to 8°C (36°F to 46°F) in the original carton to protect from light. Do not freeze. Avoid excessive shaking. Once removed from the refrigerator, Aukelso must not be exposed to temperatures above 25°C (77°F) and must be used within 30 days. Discard Aukelso if not used within the 30 days. Do not use Aukelso after the expiry date printed on the label.

Recommended Dosage: See Prescribing Information

KR/DRUGS/KTK/28D/07/2006

Manufactured by: Biocon Biologics Inc., 245 Main St 2nd Floor, Cambridge, MA 02142, U.S.A, US License No. 2324

Product of India